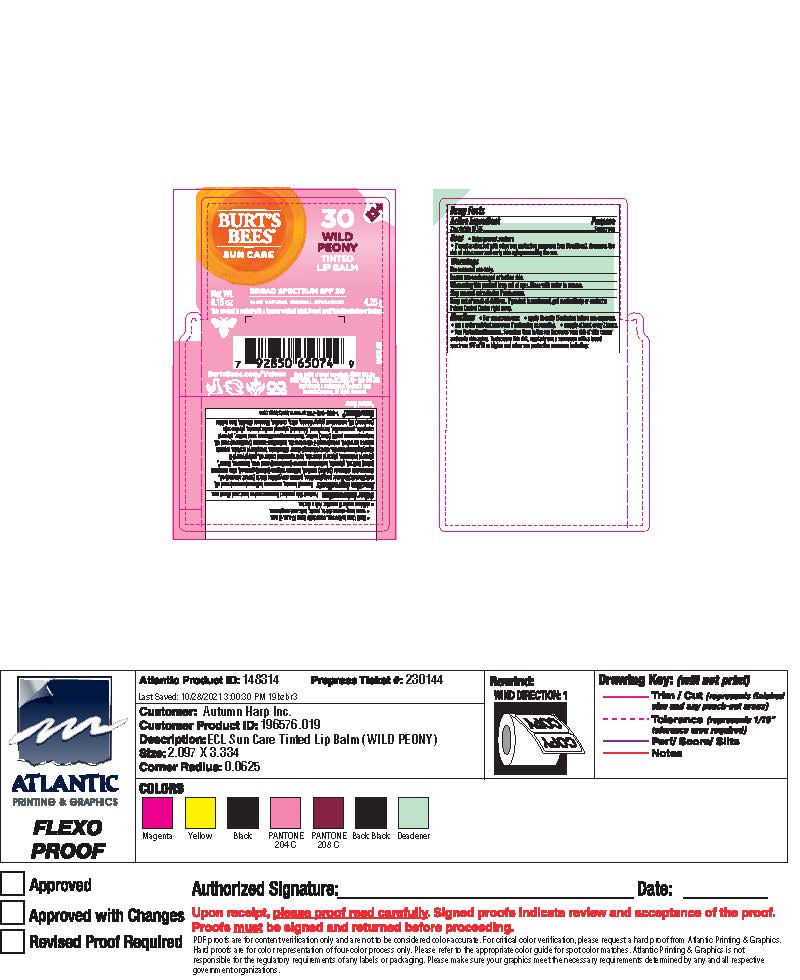 DRUG LABEL: Tinted Lip Balm SPF30 Wild Peony
NDC: 51514-0357 | Form: STICK
Manufacturer: Autumn Harp
Category: otc | Type: HUMAN OTC DRUG LABEL
Date: 20230110

ACTIVE INGREDIENTS: ZINC OXIDE 19 g/100 g
INACTIVE INGREDIENTS: TITANIUM DIOXIDE; MICA; YELLOW WAX; AMMONIUM GLYCYRRHIZATE; HYDROGENATED CASTOR OIL; BIS-OCTYLDODECYL DIMER DILINOLEATE/PROPANEDIOL COPOLYMER; SHEA BUTTER; THEOBROMA GRANDIFLORUM SEED BUTTER; GLYCERYL STEARATE SE; GLYCERYL 1-UNDECYLENATE; POLYGLYCERYL-2 DIPOLYHYDROXYSTEARATE; CASTOR OIL; SUNFLOWER OIL; .ALPHA.-TOCOPHEROL ACETATE; POLYGLYCERYL-3 DIISOSTEARATE; ARGAN OIL; ALMOND OIL; ISOAMYL LAURATE; HELIANTHUS ANNUUS SEED WAX; FERRIC OXIDE YELLOW; GLYCERYL MONOBEHENATE; GLYCERIN; SOYBEAN OIL; SESAME OIL; GLYCERYL CAPRYLATE; VANILLA BEAN; OLIVE OIL; COCONUT; JOJOBA OIL; WHEAT GERM OIL; MEDIUM-CHAIN TRIGLYCERIDES; TOCOPHEROL

Tinted Lip Balm SPF30 Wild Peony

Drug Facts

Active Ingredient

Zinc Oxide 19.5%

Purpose

Sunscreen

Uses

- Helps prevent sunburn
- If used as directed with other sun protection measures (see Directions) decreases the risk of skin cancer and early skin aging caused by the sun.

Warnings

For external use only.

Do not use on damaged or broken skin.

When using this product keep out of eyes. Rinse with water to remove.

Stop use and ask a doctor if rash occurs.

Directions

- For sunscreen use
- Apply liberally 15 minutes before sun exposure
- Use a water resistant sunscreen if swimming or sweating
- Reapply at least every 2 hours
- Sun Protection Measures: Spending time in the sun increases your risk of skin cancer and early skin aging. To decrease this risk, regularly use a sunscreen with a broad spectrum SPF of 15 or higher and other sun protection measures including:
  - limit time in the sun, especially from 10 a.m. - 2 p.m.
  - wear long-sleeve shirts, pants, hats and sunglasses.

- children under 6 months: Ask a doctor

Other Information

Protect this product from excessive heat and direct sun.

Inactive Ingredients

Isoamyl Laurate, Sesamum Indicum (Sesame) Seed Oil, Oleic/Linoleic/Linolenic Polyglycerides, Prunus Amygdalus Dulcis (Sweet Almond) Oil, Simmondsia Chinensis (Jojoba) Seed Oil, Triticum Vulgare (Wheat) Germ Oil, Olea Europaea (Olive) Fruit Oil, Ricinus Communis (Castor) Seed Oil, Glycerin, Helianthus Annuus (Sunflower) Seed Wax, Beeswax, Flavor*, Glyceryl Behenate, Glyceryl Stearate, Hydrogenated Castor Oil, Polyglyceryl-2 Dipolyhydroxystearate, Dioctyldecyl Dimer Dilinoleate, Tocopheryl Acetate, Argania Spinosa Kernel Oil, Polyglyceryl-3 Diisostearate, Helianthus Annuus (Sunflower) Seed Oil, Butyrospermum Parkii (Shea) Butter, Theobroma Grandiflorum Seed Butter, Glyceryl Caprylate, Propanediol, Tocopherol, Bisabolol, Glyceryl Undecylenate, Glycine Soja (Soybean) Oil, Ammonium Glycyrrhizate, Mica, Carmine, Titanium dioxide, Iron Oxides.

* Natural Flavor

Questions?

1-800-849-7112 or www.burtsbees.com

INDICATIONS AND USAGE

Helps prevent sunburn

Apply as needed

For external use only

Do not use on damaged or broken skin

PACKAGE LABEL

image components